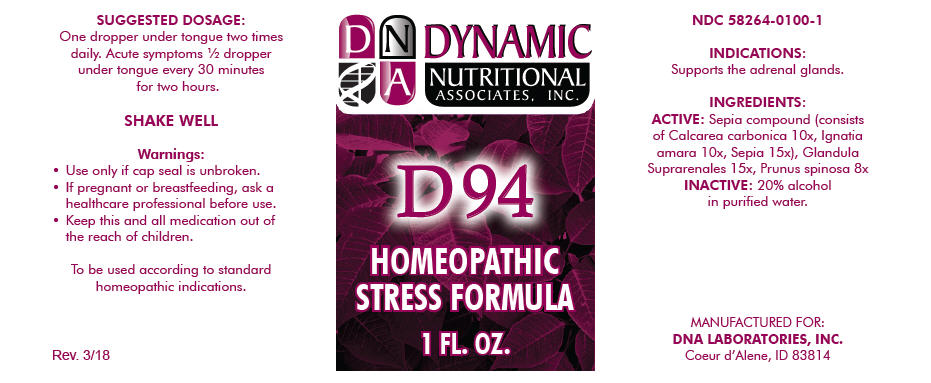 DRUG LABEL: D-94
NDC: 58264-0100 | Form: SOLUTION
Manufacturer: DNA Labs, Inc.
Category: homeopathic | Type: HUMAN OTC DRUG LABEL
Date: 20250113

ACTIVE INGREDIENTS: OYSTER SHELL CALCIUM CARBONATE, CRUDE 10 [hp_X]/1 mL; STRYCHNOS IGNATII SEED 10 [hp_X]/1 mL; SEPIA OFFICINALIS JUICE 15 [hp_X]/1 mL; BOS TAURUS ADRENAL GLAND 15 [hp_X]/1 mL; PRUNUS SPINOSA FLOWER BUD 8 [hp_X]/1 mL
INACTIVE INGREDIENTS: ALCOHOL; WATER

D-94

NDC 58264-0100-1

INDICATIONS

PURPOSE

Supports the adrenal glands.

INGREDIENTS

ACTIVE

Sepia compound (consists of Calcarea carbonica 10x, Ignatia amara 10x, Sepia 15x), Glandula Suprarenales 15x, Prunus spinosa 8x

INACTIVE

20% alcohol in purified water.

SUGGESTED DOSAGE

One dropper under tongue two times daily. Acute symptoms ½ dropper under tongue every 30 minutes for two hours.

STORAGE AND HANDLING

SHAKE WELL

Warnings

- Use only if cap seal is unbroken.

PREGNANCY OR BREAST FEEDING

- If pregnant or breastfeeding, ask a healthcare professional before use.

KEEP OUT OF REACH OF CHILDREN

- Keep this and all medication out of the reach of children.

To be used according to standard homeopathic indications.

PRINCIPAL DISPLAY PANEL - 1 FL. OZ. Bottle Label

DYNAMIC
NUTRITIONAL
ASSOCIATES, INC.

D 94

HOMEOPATHIC
STRESS FORMULA

1 FL. OZ.